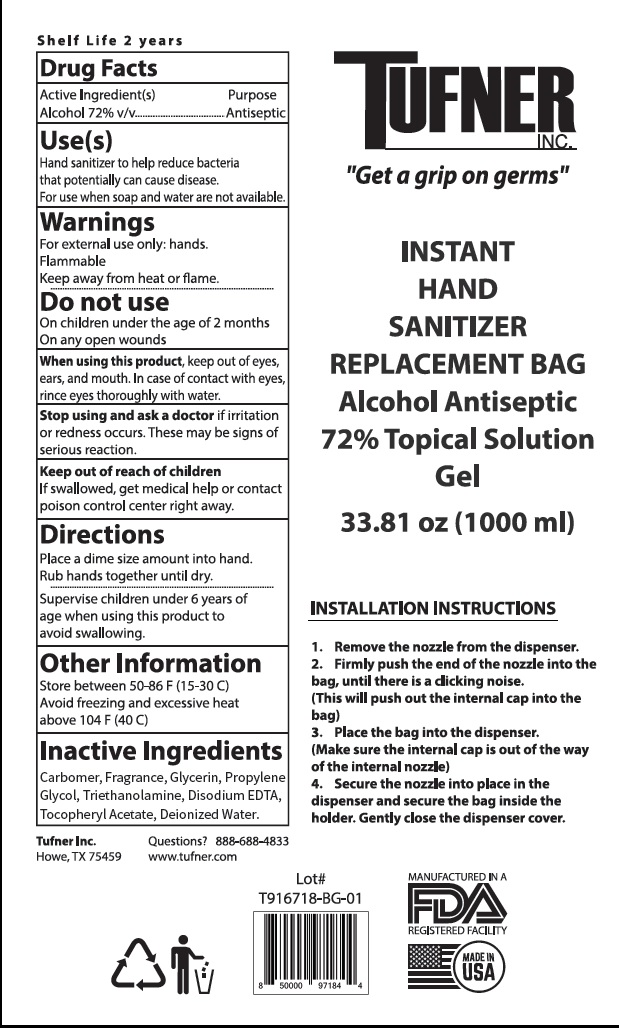 DRUG LABEL: HAND SANITIZER
NDC: 75613-010 | Form: GEL
Manufacturer: Ningbo Lanzi Cosmetic Technology Co., Ltd
Category: otc | Type: HUMAN OTC DRUG LABEL
Date: 20201024

ACTIVE INGREDIENTS: ALCOHOL 72 mL/100 mL
INACTIVE INGREDIENTS: WATER; PROPYLENE GLYCOL; EDETATE DISODIUM; TROLAMINE; .ALPHA.-TOCOPHEROL ACETATE, D-; GLYCERIN

HAND SANITIZER

Active ingredient

Ethyl Alcohol 72% v/v

Purpose

Antiseptic

Use

Hand sanitizer to Helps reduce bacteria that potentially can cause disease.

For use when soap and water are not available.

Warnings

For external use only: hands.

Flammable. Keep away from heat or flame.

Do not use

On children under the age of 2 months. On any open wounds.

When using this product

Keep out of eyes, ears, and mouth. In case of eye contact, rinse eyes thoroughly with water.

Stop use and ask a doctor if irritation or redness occurs. These may be signs of serious reaction.

Other Information:

Store between 50-86℉ (15-30℃) 。

Avoid freezing and excessive heat above 104℉ (40℃).

Keep out of reach of children.

If swallowed, get medical help or contact a Poison Control Center right away.

Directions

Place a dime size amount into hand. Rub hands together until dry.
Supervise children under 6 years of age when using this product to avoid swallwing.

Inactive ingredients

Carbmer, Fragrance, Glycerin, Propylene Glycol, Triethanolamine, Disodium ETDA, Tocopheryl Acetate, Deionized Water